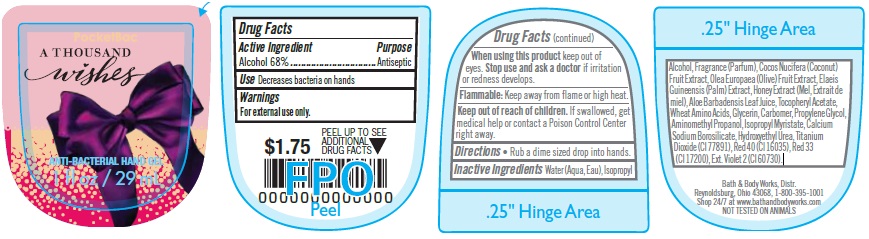 DRUG LABEL: Anti-Bacterial Hand
NDC: 62670-5003 | Form: GEL
Manufacturer: Bath & Body Works, Inc.
Category: otc | Type: HUMAN OTC DRUG LABEL
Date: 20151231

ACTIVE INGREDIENTS: ALCOHOL 68 mL/100 mL
INACTIVE INGREDIENTS: WATER

ACTIVE INGREDIENT

Alcohol 68%

PURPOSE

Antiseptic

USE

Decreases bacteria on hands.

WARNINGS

For external use only.

WHEN USING THIS PRODUCT

keep out of eyes.

STOP USE AND ASK A DOCTOR

if irritation or redness develops.

FLAMMABLE

Keep away from flame or high heat.

KEEP OUT OF REACH OF CHILDREN

If swallowed, get medical help or contact a Poison Control Center right away.

DIRECTIONS

- Rub a dime sized drop into hands.

INACTIVE INGREDIENTS

Water (Aqua, Eau), Isopropyl Alcohol, Fragrance (Parfum), Cocos Nucifera (Coconut) Fruit Extract, Olea Europaea (Olive) Fruit Extract, Elaeis Guineensis (Palm) Extract, Honey Extract (Mel, Extrait de miel), Aloe Barbadensis Leaf Juice, Tocopheryl Acetate, Wheat Amino Acids, Glycerin, Carbomer, Propylene Glycol, Aminomethyl Propanol, Isopropyl Myristate, Calcium Sodium Borosilicate, Hydroxyethyl Urea, Titanium Dioxide (CI 77891), Red 40 (CI 16035), Red 33 (CI 17200), Ext. Violet 2 (CI 60730).

COMPANY INFORMATION

Bath & Body Works, Distr.

Reynoldsburg, Ohio 43068

1-800-395-1001

www.bathandbodyworks.com